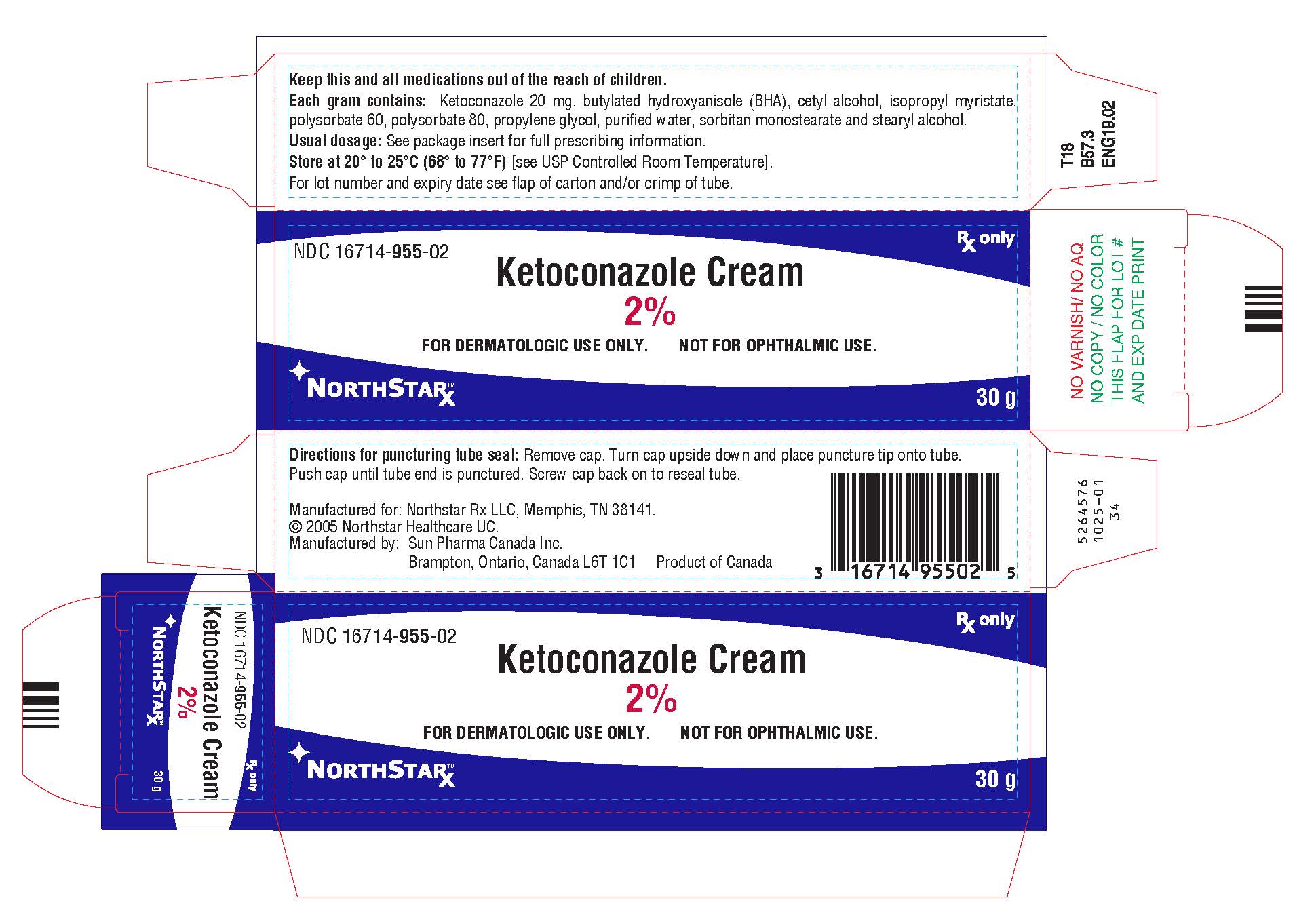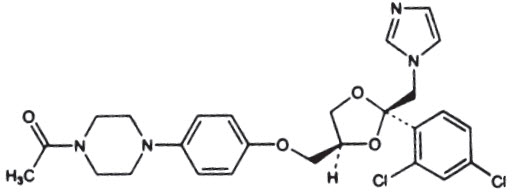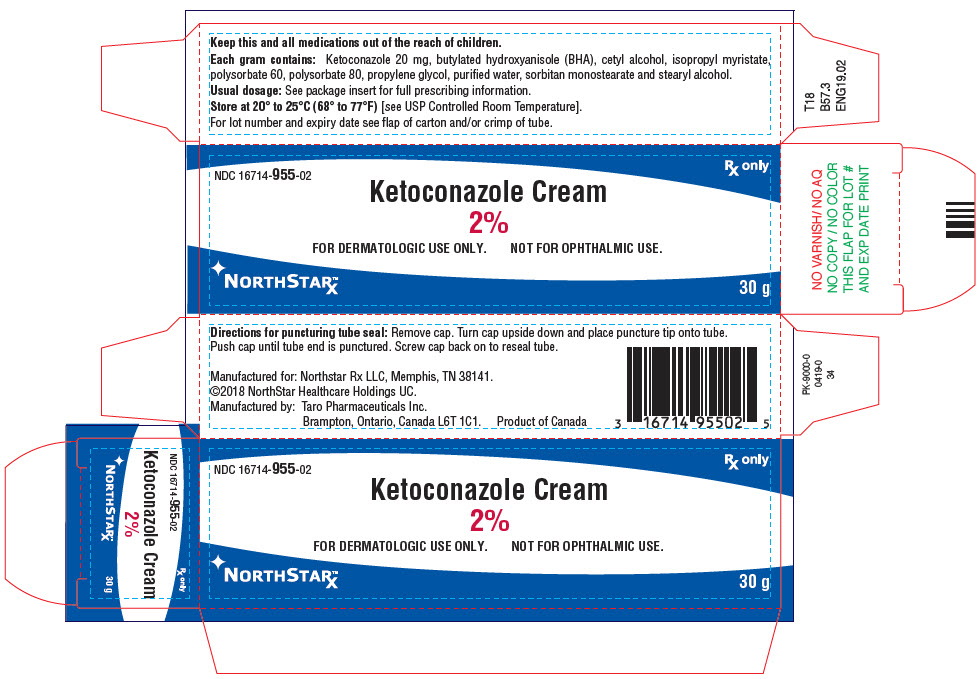 DRUG LABEL: Ketoconazole
NDC: 16714-955 | Form: CREAM
Manufacturer: NORTHSTAR RX LLC
Category: prescription | Type: HUMAN PRESCRIPTION DRUG LABEL
Date: 20260126

ACTIVE INGREDIENTS: KETOCONAZOLE 20 mg/1 g
INACTIVE INGREDIENTS: BUTYLATED HYDROXYANISOLE; CETYL ALCOHOL; ISOPROPYL MYRISTATE; POLYSORBATE 60; POLYSORBATE 80; PROPYLENE GLYCOL; WATER; SORBITAN MONOSTEARATE; STEARYL ALCOHOL

Ketoconazole
Cream, 2%

Rx only

DESCRIPTION

Ketoconazole cream, 2% contains the broad-spectrum synthetic antifungal agent, ketoconazole 2%, formulated in an aqueous cream vehicle consisting of butylated hydroxyanisole (BHA), cetyl alcohol, isopropyl myristate, polysorbate 60, polysorbate 80, propylene glycol, purified water, sorbitan monostearate and stearyl alcohol.

Ketoconazole is cis-1-acetyl-4-[4-[[2-(2,4-dichlorophenyl)-2-(1 H-imidazol-1-ylmethyl)-1,3-dioxolan-4-yl]methoxy]phenyl] piperazine and has the following structural formula:

Molecular Formula: C26H28Cl2N4O4

Molecular Weight: 531.43

CLINICAL PHARMACOLOGY

When ketoconazole cream, 2% was applied dermally to intact or abraded skin of beagle dogs for 28 consecutive days at a dose of 80 mg, there were no detectable plasma levels using an assay method having a lower detection limit of 2 ng/mL.

After a single topical application to the chest, back and arms of normal volunteers, systemic absorption of ketoconazole was not detected at the 5 ng/mL level in blood over a 72-hour period.

Two dermal irritancy studies, a human sensitization test, a phototoxicity study and a photoallergy study conducted in 38 male and 62 female volunteers showed no contact sensitization of the delayed hypersensitivity type, no irritation, no phototoxicity and no photoallergenic potential due to ketoconazole cream, 2%.

Microbiology

Ketoconazole is a broad spectrum synthetic antifungal agent which inhibits the in vitrogrowth of the following common dermatophytes and yeasts by altering the permeability of the cell membrane: dermatophytes: Trichophyton rubrum, T. mentagrophytes, T. tonsurans, Microsporum canis, M. audouini, M. gypseumand Epidermophyton floccosum; yeasts: Candida albicans, Malassezia ovale (Pityrosporum ovale)and C. tropicalis;and the organism responsible for tinea versicolor, Malassezia furfur (Pityrosporum orbiculare).Only those organisms listed in the INDICATIONS AND USAGE section have been proven to be clinically affected. Development of resistance to ketoconazole has not been reported.

Mode of Action

In vitro studies suggest that ketoconazole impairs the synthesis of ergosterol, which is a vital component of fungal cell membranes. It is postulated that the therapeutic effect of ketoconazole in seborrheic dermatitis is due to the reduction of M. ovale, but this has not been proven.

INDICATIONS AND USAGE

Ketoconazole cream, 2% is indicated for the topical treatment of tinea corporis, tinea cruris and tinea pedis caused by Trichophyton rubrum, T. mentagrophytesand Epidermophyton floccosum; in the treatment of tinea (pityriasis) versicolor caused by Malassezia furfur (Pityrosporum orbiculare); in the treatment of cutaneous candidiasis caused by Candida spp.and in the treatment of seborrheic dermatitis.

CONTRAINDICATIONS

Ketoconazole cream, 2% is contraindicated in persons who have shown hypersensitivity to the active or excipient ingredients of this formulation.

WARNINGS

Ketoconazole cream, 2% is not for ophthalmic use.

PRECAUTIONS

General

If a reaction suggesting sensitivity or chemical irritation should occur, use of the medication should be discontinued. Hepatitis (1:10,000 reported incidence) and, at high doses, lowered testosterone and ACTH induced corticosteroid serum levels have been seen with orally administered ketoconazole; these effects have not been seen with topical ketoconazole.

Carcinogenesis, Mutagenesis, Impairment of Fertility

A long-term feeding study in Swiss Albino mice and in Wistar rats showed no evidence of oncogenic activity. The dominant lethal mutation test in male and female mice revealed that single oral doses of ketoconazole as high as 80 mg/kg produced no mutation in any stage of germ cell development. The Ames' salmonellamicrosomal activator assay was also negative.

Pregnancy:

Teratogenic effects:

Pregnancy Category C:

Ketoconazole has been shown to be teratogenic (syndactylia and oligodactylia) in the rat when given orally in the diet at 80 mg/kg/day, (10 times the maximum recommended human oral dose). However, these effects may be related to maternal toxicity, which was seen at this and higher dose levels.

There are no adequate and well-controlled studies in pregnant women. Ketoconazole should be used during pregnancy only if the potential benefit justifies the potential risk to the fetus.

Nursing Mothers

It is not known whether ketoconazole cream, 2% administered topically could result in sufficient systemic absorption to produce detectable quantities in breast milk. Nevertheless, a decision should be made whether to discontinue nursing or discontinue the drug, taking into account the importance of the drug to the mother.

Pediatric Use

Safety and effectiveness in children have not been established.

ADVERSE REACTIONS

During clinical trials 45 (5.0%) of 905 patients treated with ketoconazole cream, 2% and 5 (2.4%) of 208 patients treated with placebo reported side effects consisting mainly of severe irritation, pruritus and stinging. One of the patients treated with ketoconazole cream developed a painful allergic reaction.

In worldwide postmarketing experience, rare reports of contact dermatitis have been associated with ketoconazole cream or one of its excipients, namely propylene glycol.

To report SUSPECTED ADVERSE REACTIONS, contact Northstar RxLLC at 1-800-206-7821 and/or FDA at 1-800-FDA-1088 or www.fda.gov/medwatch.

DOSAGE AND ADMINISTRATION

Cutaneous candidiasis, tinea corporis, tinea cruris, tinea pedis, and tinea (pityriasis) versicolor

It is recommended that ketoconazole cream, 2% be applied once daily to cover the affected and immediate surrounding area. Clinical improvement may be seen fairly soon after treatment is begun; however, candidal infections and tinea cruris and corporis should be treated for two weeks in order to reduce the possibility of recurrence.

Patients with tinea versicolor usually require two weeks of treatment. Patients with tinea pedis require six weeks of treatment.

Seborrheic dermatitis

Ketoconazole cream, 2% should be applied to the affected area twice daily for four weeks or until clinical clearing.

If a patient shows no clinical improvement after the treatment period, the diagnosis should be redetermined.

HOW SUPPLIED

Ketoconazole cream, 2% is supplied in 15 g (NDC 16714-955-01), 30 g (NDC 16714-955-02), and 60 g (NDC 16714-955-03) tubes.

STORAGE AND HANDLING

Store at 20° to 25°C (68° to 77°F) [see USP Controlled Room Temperature].

Manufactured for: Northstar RxLLC, Memphis, TN 38141.
Toll Free: 1-800-206-7821
Manufactured by: Sun Pharma Canada Inc., Brampton, Ontario, Canada L6T 1C1.

Revised: September 2025
5264904-0925-01 41

PRINCIPAL DISPLAY PANEL - 30 g Tube Carton

NDC 16714-955-02
Rx only

Ketoconazole Cream 2%
FOR DERMATOLOGIC USE ONLY.
NOT FOR OPHTHALMIC USE.

NORTHSTARX™
30 g